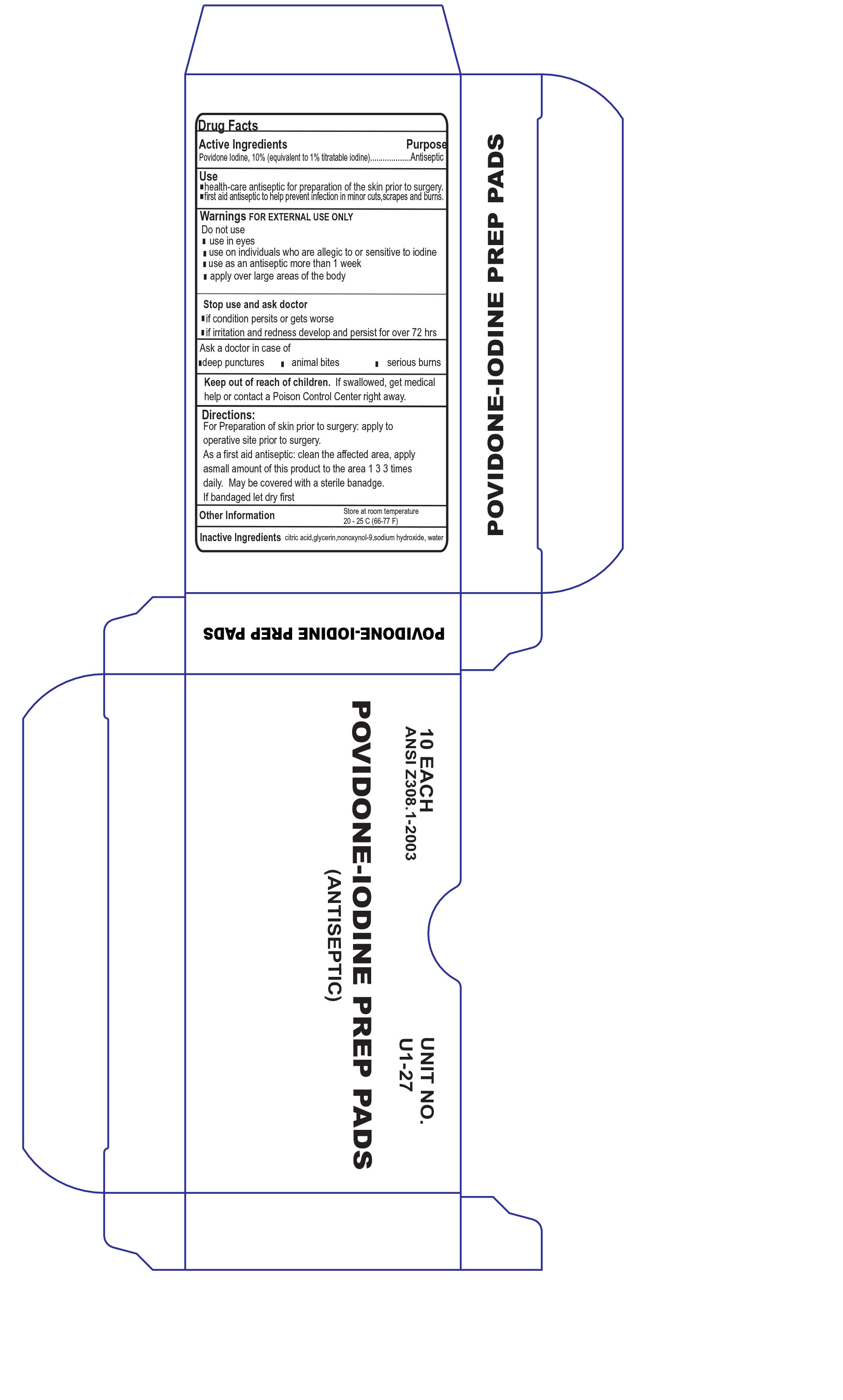 DRUG LABEL: Povidone Iodine Prep Pads
NDC: 68183-119 | Form: CLOTH
Manufacturer: Custom Kits Company Inc
Category: otc | Type: HUMAN OTC DRUG LABEL
Date: 20200117

ACTIVE INGREDIENTS: POVIDONE-IODINE 10 g/1 mL
INACTIVE INGREDIENTS: NONOXYNOL-9; WATER

Povidone Iodine Prep Pad

Active Ingredient

Povidone Iodine 10%

Purpose

Antiseptic

Uses

Antiseptic cleanser to help prevent skin infection in minor cuts, scrapes and burns.

For preparation of the skin prior to surgery

Helps reduct bacteria that can potentially cause skin infection

Warnings

For External Use Only

Do Not Use

In the eyes

As a first aid antiseptic for more than 1 week

Over large areas of the body

Ask doctor before use if you have

Deep or puncuture wounds

Animal bites

Serious wounds

Stop Use and ask doctor if

Condition worsens or persists for more than 72 hours

Irritation and rednes develops

Keep Out of the reach of Children

If swallowed, get medical help or contact a Poson Control Center immediately

Directions

Tear at notch

Remove applicator

Use only once

As a first aid antiseptic - Clean affected area

apply 1 to 3 times daily

May be covered with a sterile bandage

If bandaged let dry first

OTHER SAFETY INFORMATION

Store at room temperature

Avoid excessive heat

Inactive ingredient

nonoxynol-9, water